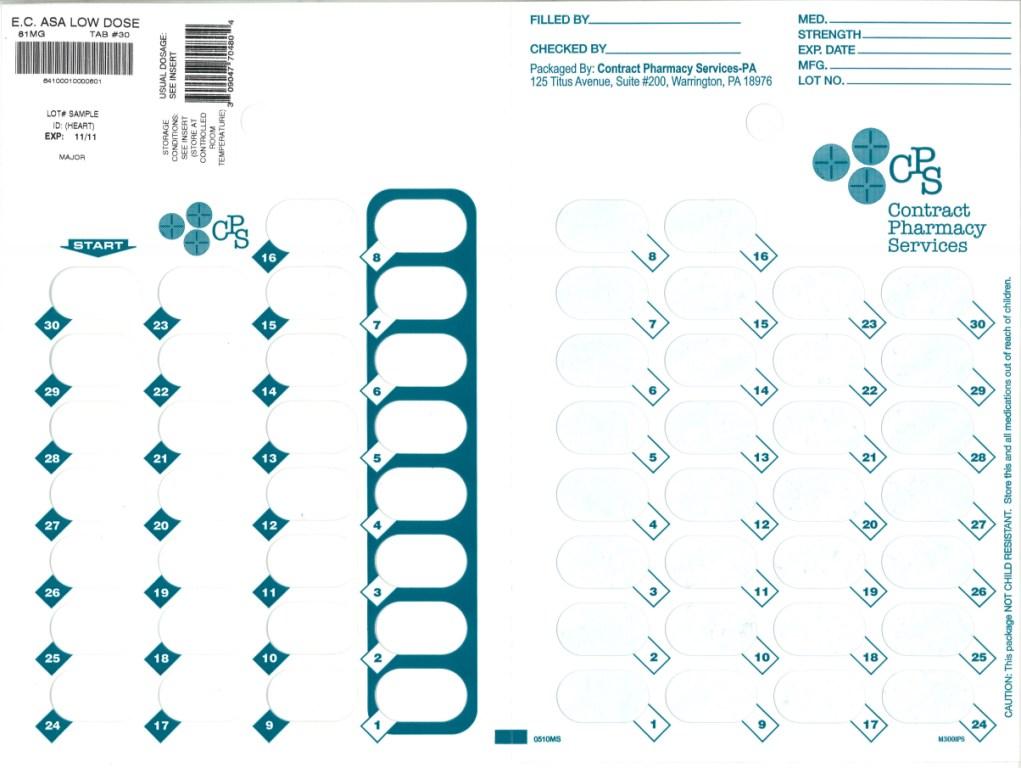 DRUG LABEL: ASPIRIN LOW DOSE
NDC: 67046-168 | Form: TABLET, FILM COATED
Manufacturer: Contract Pharmacy Services-PA
Category: otc | Type: HUMAN OTC DRUG LABEL
Date: 20100930

ACTIVE INGREDIENTS: ASPIRIN 81 mg/1 1
INACTIVE INGREDIENTS: ANHYDROUS LACTOSE; CARNAUBA WAX; SILICON DIOXIDE; CROSCARMELLOSE SODIUM; D&C YELLOW NO. 10; IRON; METHACRYLIC ACID - ETHYL ACRYLATE COPOLYMER (1:1) TYPE A; CELLULOSE, MICROCRYSTALLINE; POLYSORBATE 80; DIMETHICONE; SODIUM HYDROXIDE; SODIUM LAURYL SULFATE; TALC; TITANIUM DIOXIDE

Aspirin Low Tablets

ACTIVE INGREDIENT (IN EACH TABLET)

Aspirin 81 mg (NSAID*)

*nonsteroidal anti-inflammatory drug

PURPOSE

Pain reliever

USES

- for the temporary relief of minor aches and pains or as recommended by your doctor. Because of its delayed action, this product may not provide fast relief of headache or other symptoms needing immediate relief.
- ask your doctor about other uses for this product

WARNINGS

Reye’s syndrome: Children and teenagers who have or are recovering from chicken pox or flu-like symptoms should not use this product. When using this product, if changes in behavior with nausea and vomiting occur, consult a doctor because these symptoms could be an early sign of Reye’s syndrome, a rare but serious illness.

Allergy alert: Aspirin may cause a severe allergic reaction which may include:

- hives
- facial swelling
- asthma (wheezing)
- shock

Stomach bleeding warning: This product contains a nonsteroidal anti-inflammatory drug (NSAID), which may cause severe stomach bleeding. The chance is higher if you

- are age 60 or older
- have had stomach ulcers or bleeding problems
- take a blood thinning (anticoagulant) or steroid drug
- take other drugs containing prescription or nonprescription NSAIDs (aspirin, ibuprofen, naproxen, or others)
- have 3 or more alcoholic drinks every day while using this product
- take more or for a longer time than directed

Do not use

• if you are allergic to aspirin or any other pain reliever/fever reducer

Ask a doctor before use if

- stomach bleeding warning applies to you
- you have a history of stomach problems, such as heartburn
- you have high blood pressure, heart disease, liver cirrhosis, or kidney disease
- you are taking a diuretic

Ask a doctor or pharmacist before use if

taking a prescription drug for diabetes, gout or arthritis

Stop use and ask a doctor if

- you experience any of the following signs of stomach bleeding:
- feel faint
- vomit blood
- have bloody or black stools
- have stomach pain that does not get better
- pain gets worse or lasts for more than 10 days
- redness or swelling is present
- any new symptoms appear
- ringing in the ears or loss of hearing occurs

If pregnant or breast-feeding,

ask a health professional before use. It is especially important not to use aspirin during the last 3 months of pregnancy unless definitely directed to do so by a doctor because it may cause problems in the unborn child or complications during delivery.

Keep out of reach of children.

Overdose warning: Taking more than the recommended dose (overdose) may cause liver damage. In case of overdose, get medical help or contact a Poison Control Center right away. (1-800-222-1222). Quick medical attention is critical for adults as well as for children even if you do not notice any signs or symptoms.

DIRECTIONS

- drink a full glass of water with each dose
- do not exceed recommended dosage
- adults and children 12 years and over: take 4 to 8 tablets every 4 hours not to exceed 48 tablets in 24 hours unless directed by a doctor
- children under 12 years: ask a doctor

OTHER INFORMATION

store at 20° to 25°C (68° to 77°F)

Inactive Ingredients

anhydrous lactose, carnauba wax, colloidal silicon dioxide, croscarmellose sodium, D-C yellow #10 aluminum lake, iron oxide ochre, methacrylic acid copolymer, microcrystalline cellulose, polysorbate 80, simethicone, sodium hydroxide, sodium lauryl sulfate, talc, titanium dioxide

QUESTIONS OR COMMENTS?

Distributed by:

Major Pharmaceuticals

31778 Enterprise Drive

Livonia, MI 48150

Repackaged by:
Contract Pharmacy Services-PA
125 Titus Ave Suite 200
Warrington, PA 18976 USA

Original--08/2010--NJW

Package Label

Blister of 30 Tablets